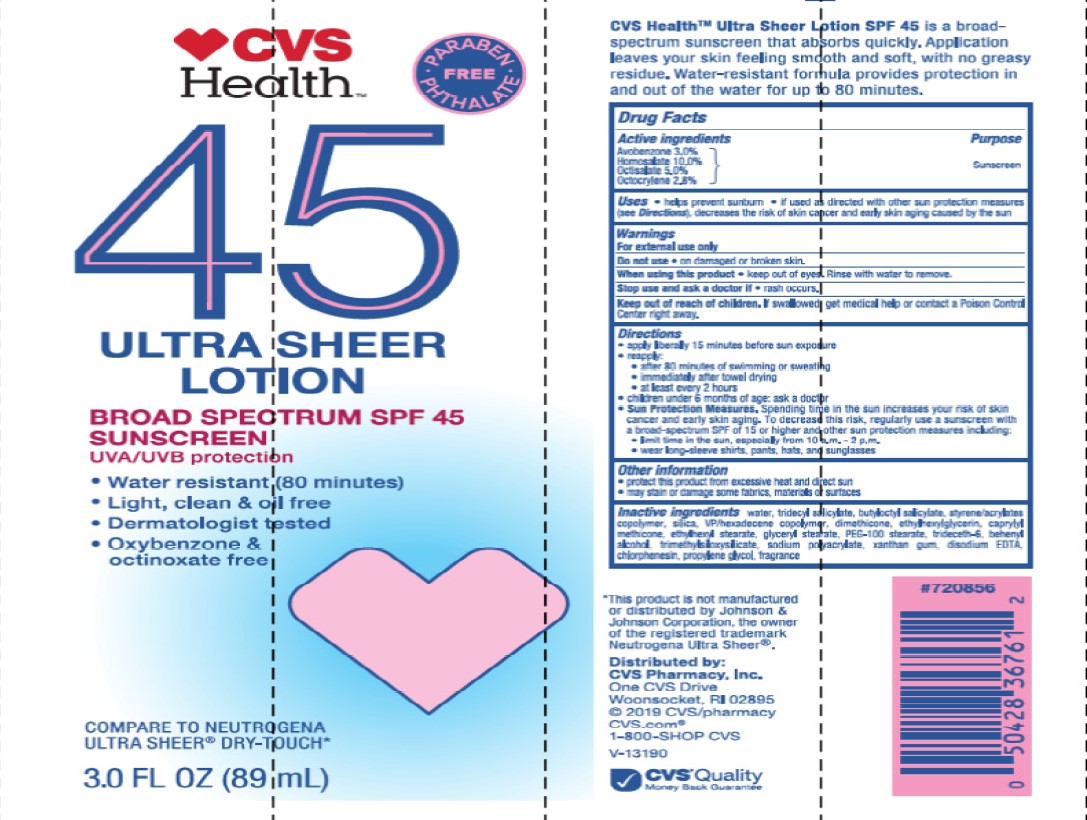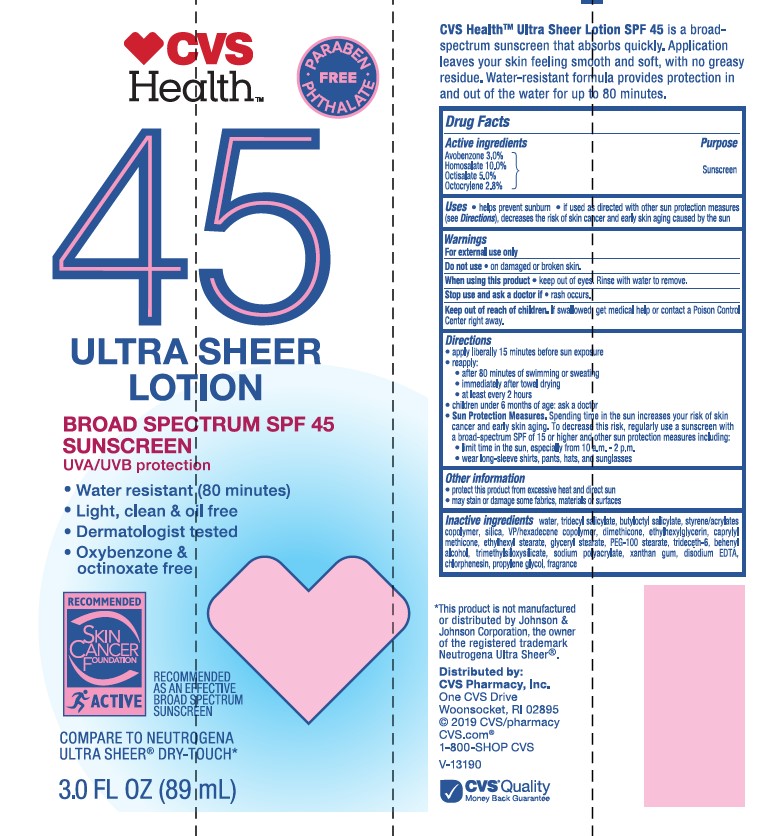 DRUG LABEL: CVS Health Ultra Sheer Broad Spectrum SPF 45 Sunscreen
NDC: 69842-341 | Form: LOTION
Manufacturer: CVS Pharmacy
Category: otc | Type: HUMAN OTC DRUG LABEL
Date: 20241022

ACTIVE INGREDIENTS: OCTOCRYLENE 28 mg/1 mL; OCTISALATE 50 mg/1 mL; HOMOSALATE 100 mg/1 mL; AVOBENZONE 30 mg/1 mL
INACTIVE INGREDIENTS: PROPYLENE GLYCOL; CAPRYLYL TRISILOXANE; EDETATE DISODIUM; METHYLPARABEN; TRIDECETH-6; TRIMETHYLSILOXYSILICATE (M/Q 0.8-1.0); HEXADECYL POVIDONE; TRIDECYL SALICYLATE; XANTHAN GUM; ETHYLHEXYL STEARATE; CHLORPHENESIN; ETHYLHEXYLGLYCERIN; DIMETHICONE; WATER; BUTYLOCTYL SALICYLATE; BUTYL METHACRYLATE/METHYL METHACRYLATE/METHACRYLIC ACID/STYRENE CROSSPOLYMER; SILICON DIOXIDE; DOCOSANOL; GLYCERYL STEARATE/PEG-100 STEARATE; SODIUM POLYACRYLATE (8000 MW); PROPYLPARABEN

CVS Health Ultra Sheer Lotion Broad Spectrum SPF 45 Sunscreen

Active ingredients

Avobenzone 3.0%, Homosalate 10.0%, Octisalate 5.0%, Octocrylene 2.8%

Purpose

Sunscreen

Uses

- helps prevent sunburn
- if used as directed with other sun protection measures (see Directions), decreases the risk of skin cancer and early skin aging caused by the sun

Warnings

For external use only

Do not use

- on damaged or broken skin.

When using this product

- keep out of eyes. Rinse with water to remove.

Stop use and ask a doctor

- if rash occurs.

Keep out of reach of children.

If product is swallowed, get medical help or contact a Poison Control Center right away.

Directions

• apply liberally 15 minutes before sun exposure
reapply:
• after 80 minutes of swimming or sweating
• immediately after towel drying
• at least every 2 hours
• children under 6 months: Ask a doctor

Sun Protection Measures. Spending time in the sun increases your risk of skin cancer and early skin aging. To decrease this risk, regularly use a sunscreen with a Broad Spectrum SPF value of 15 or higher and other sun protection measures including:
• limit time in the sun, especially from 10 a.m. - 2 p.m.
• wear long-sleeved shirts, pants, hats, and sunglasses

Other information

• protect the product in this product from excessive heat and direct sun
• may stain or damage some fabrics, materials or surfaces

Inactive ingredients

water, tridecyl salicylate, butyloctyl salicylate, styrene/acrylates copolymer, silica, VP/hexadecene copolymer, dimethicone, ethylhexylglycerin, caprylyl methicone, ethylhexyl stearate, glyceryl stearate, PEG-100 stearate, trideceth-6, behenyl alcohol, trimethylsiloxysilicate, sodium polyacrylate, xanthan gum, disodium EDTA, chlorophesin, propylene glycol, fragrance

PACKAGE LABEL

CVS Health Ultra Sheer Lotion Broad Spectrum SPF 45 Sunscreen

3.0 fl oz (89 mL)